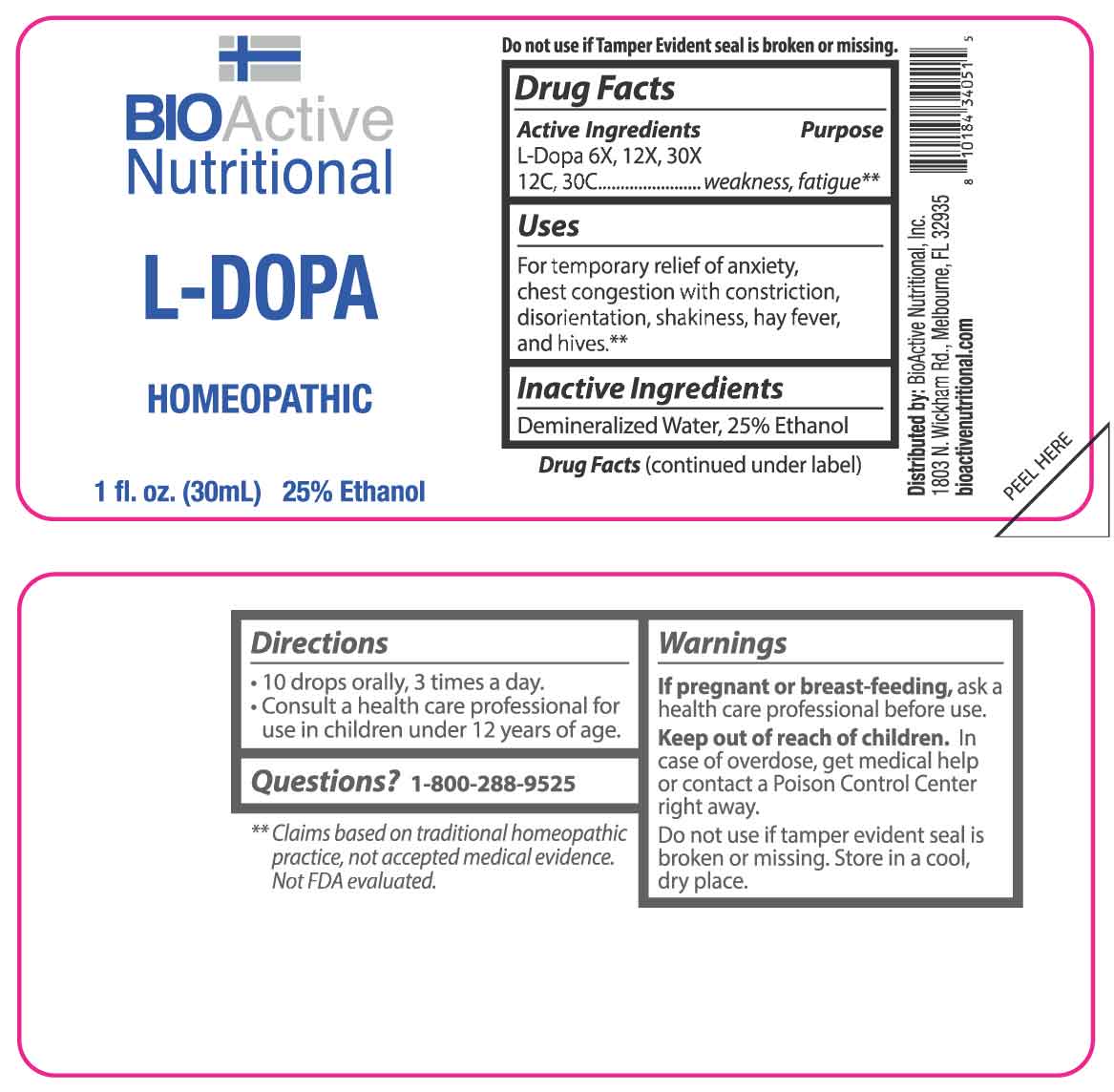 DRUG LABEL: L-Dopa
NDC: 43857-0226 | Form: LIQUID
Manufacturer: BioActive Nutritional, Inc.
Category: homeopathic | Type: HUMAN OTC DRUG LABEL
Date: 20251218

ACTIVE INGREDIENTS: LEVODOPA 6 [hp_X]/1 mL
INACTIVE INGREDIENTS: WATER; ALCOHOL

DRUG FACTS:

ACTIVE INGREDIENTS:

L-Dopa 6X, 12X, 30X, 12C, 30C.

PURPOSE:

L-Dopa - weakness, fatigue**

**Claims based on traditional homeopathic practice, not accepted medical evidence. Not FDA evaluated.

USES:

For temporary relief of anxiety, chest congestion with constriction, disorientation, shakiness, hay fever, and hives.

**Claims based on traditional homeopathic practice, not accepted medical evidence. Not FDA evaluated.

WARNINGS:

If pregnant or breast-feeding, ask a health care professional before use.

Keep out of reach of children. In case of overdose, get medical help or contact a Poison Control Center right away.

Do not use if tamper evident seal is broken or missing.

Store in a cool, dry place.

KEEP OUT OF REACH OF CHILDREN:

In case of overdose, get medical help or contact a Poison Control Center right away.

DIRECTIONS:

• 10 drops orally, 3 times a day.

• Consult a health care professional for use in children under 12 years of age.

INACTIVE INGREDIENTS:

Demineralized Water, 25% Ethanol

QUESTIONS:

Distributed by:
BioActive Nutritional, Inc.
1803 N. Wickham Rd.
Melbourne, FL 32935
bioactivenutritional.com

1-800-288-9525

PACKAGE LABEL DISPLAY:

BioActive Nutritional

L-DOPA

HOMEOPATHIC

1 fl. oz. (30 mL)